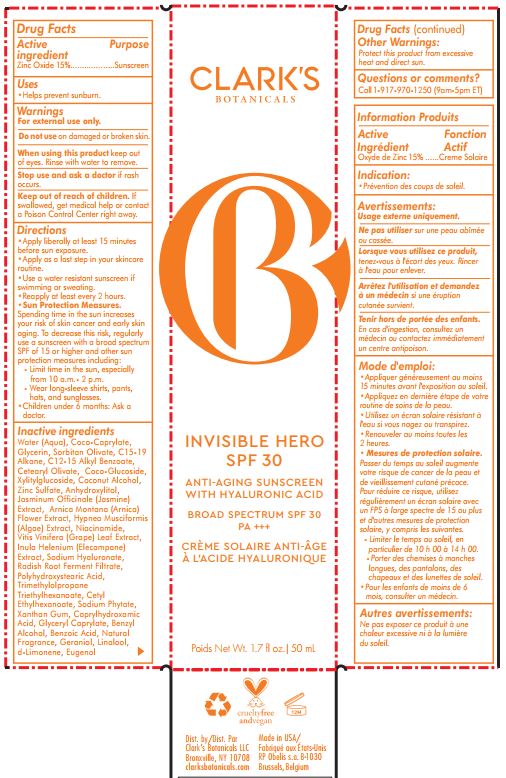 DRUG LABEL: Invisible Hero SPF30
NDC: 82071-042 | Form: LIQUID
Manufacturer: Clark's Botanicals, LLC
Category: otc | Type: HUMAN OTC DRUG LABEL
Date: 20210801

ACTIVE INGREDIENTS: ZINC OXIDE 15 g/100 mL
INACTIVE INGREDIENTS: WATER; COCO-CAPRYLATE; GLYCERIN; SORBITAN OLIVATE; C15-19 ALKANE; ALKYL (C12-15) BENZOATE; CETEARYL OLIVATE; COCO GLUCOSIDE; XYLITYLGLUCOSIDE; COCONUT ALCOHOL; ZINC SULFATE; ANHYDROXYLITOL; JASMINUM OFFICINALE FRUIT; ARNICA MONTANA FLOWER; HYPNEA MUSCIFORMIS; NIACINAMIDE; VITIS VINIFERA LEAF; INULA HELENIUM ROOT; HYALURONATE SODIUM; RADISH; POLYHYDROXYSTEARIC ACID STEARATE; TRIMETHYLOLPROPANE; CETYL ETHYLHEXANOATE; PHYTATE SODIUM; XANTHAN GUM; CAPRYLHYDROXAMIC ACID; GLYCERYL MONOCAPRYLATE; BENZYL ALCOHOL; BENZOIC ACID; GERANIOL; LINALOOL, (+/-)-; LIMONENE, (+)-; EUGENOL

Active Ingredient

Zinc Oxide, 15%

Purpose

Sunscreen

Uses

Helps prevent sunburn

Warnings

For external use only

Do not use on damaged or broken skin

When using this product keep out of eyes. Rinse with water to remove.

Stop use and ask a doctor if rash occurs

Keep out of reach of children. If swallowed, get medical help or contact a Poison Control Center right away.

Directions

- Apply liberally at least 15 minutes before sun exposure
- Apply as the last step in your skincare routine
- Use a water resistant sunscreen if swimming or sweating
- Reapply at least every 2 hours

Sun Protection Measures

Spending time in the sun increases your risk of skin cancer and early skin aging. To decrease this risk, regularly use a sunscreen with a broad spectrum SPF of 15 or higer and other sun protection measures includuing:
- Limit time in the sun, especailly from 10 AM to 2 PM
- Wear long-sleeve shirts, pants, hats, and sunglasses

- Children under 6 months: Ask a doctor

Inactive Ingredients

Water (Aqua), Coco-Caprylate, Glycerin, Sorbitan Olivate, C15-19 Alkane, C12-15 Alkyl Benzoate, Cetearyl Olivate, Coco-Glucoside, Xylitylglucoside, Coconut Alcohol, Zinc Sulfate, Anhydroxylitol, Jasminum Officinale (Jasmine) Extract, Arnica Montana (Arnica) Flower Extract, Hypnea Musciformis (Algae) Extract, Niacinamide, Vitis Vinifera (Grape) Leaf Extract, Inula Helenium (Elecampane) Extract, Sodium hyaluronate, Radish Root Ferment Filtrate, Polyhydroxystearic Acid, Trimethylolpropane Triethylhexanoate, Cetyl Ethylhexanoate, Sodium Phytate, Xanthan Gum, Caprylhydroxamic Acid, Glyceryl Caprylate, Benzyl Alcohol, Benzoic Acid, Natural Fragrance, Geraniol, Linalool, d -Limonene, Eugenol

Other Warnings

Protect this product from excessive heat and direct sun

Questions or Comments

Call 1-917-970-1250 (9 AM to 5 PM ET)

Distributed by Clark's Botanicals, LLC
Bronxville, NY
clarksbotanicals.com

PACKAGE LABEL

Clark's Botanicals
Invisible Hero SPF 30
Anti-Aging Sunscreen with Hyaluronic Acid
Broad Spectrum SPF 30 PA+++

Poids Net Wt. 1.7 fl. oz.| 50 mL